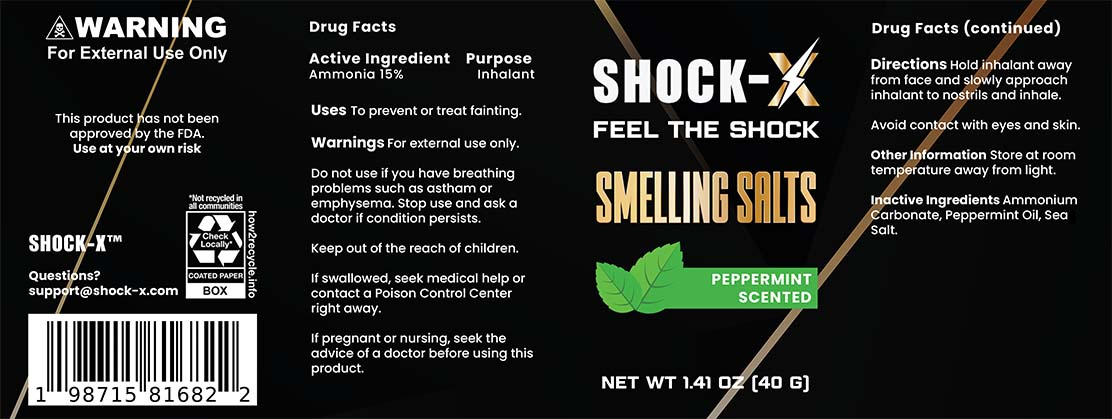 DRUG LABEL: Shock-X Ammonia Inhalant
NDC: 85570-1111 | Form: INHALANT
Manufacturer: Platinum Trident Enterprise
Category: otc | Type: HUMAN OTC DRUG LABEL
Date: 20250608

ACTIVE INGREDIENTS: AMMONIA 15 g/100 g
INACTIVE INGREDIENTS: SEA SALT; PEPPERMINT OIL; AMMONIUM CARBONATE

Active Ingredients

Ammonia (15%)

Purpose

Inhalant

Uses

To prevent or treat fainting.

Warnings

For external use only.

Do not use if you have breathing problems such as asthma or emphysema. Stop use and ask a doctor if condition persists.

Keep out of the reach of children.

OTHER SAFETY INFORMATION

If swallowed, seek medical help or contact a Poison Control Center right away.

PREGNANCY OR BREAST FEEDING

If pregnant or nursing, seek the advice of a doctor before using this product.

Directions

Hold inhalant away from face and slowly approach inhalant to nostrils and inhale. Avoid contact with eyes and skin.

Other Information

Store at room temperature away from light.

Inactive Ingredients

Alcohol, Cotton, Peppermint Oil, Water.

Questions

Contact us at support@shock-x.com